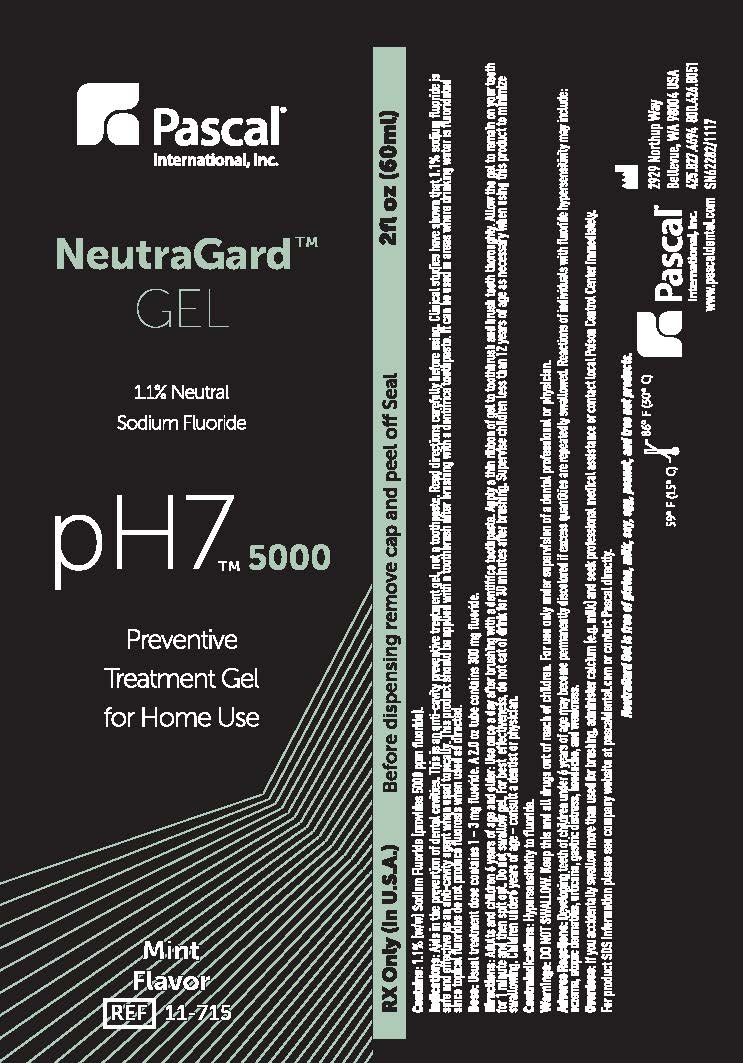 DRUG LABEL: NeutraGard Gel Mint
NDC: 10866-0110 | Form: GEL
Manufacturer: Pascal Company, Inc.
Category: prescription | Type: HUMAN PRESCRIPTION DRUG LABEL
Date: 20190130

ACTIVE INGREDIENTS: SODIUM FLUORIDE 11.28 mg/1 g
INACTIVE INGREDIENTS: WATER 942 mg/1 g

NeutraGard Gel Mint

Dosage

RX Only in USA

Before dispensing remove cap and peel off seal

Contains: 1.1% w/w Sodium fluoride (provides 5000ppm fluoride)

Usual treatment does contains 1-3 mg fluoride. A 2.0oz tube contains 300 mg of fluoride

Indications & Usage

Indications and Usage

Aids in the prevention of dental cavities. This is an anti-cavity (preventive treatment gel, not a toothpaste. Read directions carefully before using. Clinical studies have shown that 1.1% sodium fluoride is safe and effective as an anti-cavity agent when used topically. This product should be applied with a toothbrush after brushing with a dentifrice toothpaste. It can be used in areas where drinking water is fluoridated since topical fluorides do not produce fluorosis when used as directed.

Adults and children 6 years of age and older: Use once daily after brushing with a dentifrice toothpaste. Apply a thin ribbon of gel to toothbrush and brush teeth thoroughly. Allow the gel to reamin on your teeth for 1 minute and then spit out. Do not swallow gel. For best effectiveness, do not eat or drink for 30 minutes after brushing. Supervise children less than 12 years of age as necessary when using this product to minimize swallowing.

Children under 6 years of age - consult a dentist or physician.

Contraindications

Hypersensitivity to fluoride

Warnings & Precautions

Do not swallow.

Keep this and all drugs out of reach of children.

For use only under supervision of a dental professional or physician.

Adverse Reactions: Developing teeth of children under 6 years of age may become permanently discolored if excess quantities are repeatedly swallowed. Reactions of individuals whith fluoride hypersensitivity amy include: eczema, atopic dermatitis, uticaria, gastric distress, headache, and weakness.

Overdose: If you accidentally swallow more than used for brushing, administer calcium (e.g. milk) and seek professional medical assistance or contact local Poison Control Center immediately.

For product SDS information, please see company website at pascaldental.com or contact Pascal directly.

Neutragard Gel is free of gluten, milk, soy, egg, peanut and tree nut products.

Store product between 59-86ºF (15-30ºC)

NeutraGard Gel 1.1% Neutral Sodium Fluoride Gel Mint

pH7 5000

Preventive Treatment Gel for Home Use

Mint Flavor

REF 11-715